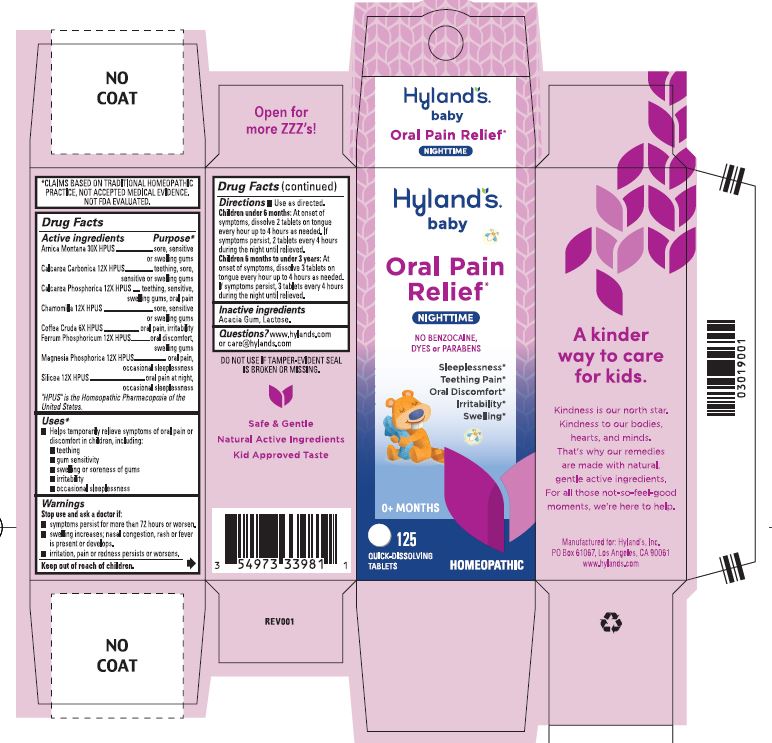 DRUG LABEL: Baby Nighttime Oral Pain Relief
NDC: 54973-3324 | Form: TABLET
Manufacturer: Hyland' Inc.
Category: homeopathic | Type: HUMAN OTC DRUG LABEL
Date: 20250317

ACTIVE INGREDIENTS: OYSTER SHELL CALCIUM CARBONATE, CRUDE 12 [hp_X]/1 g; TRIBASIC CALCIUM PHOSPHATE 12 [hp_X]/1 g; MATRICARIA CHAMOMILLA 12 [hp_X]/1 g; SILICON DIOXIDE 12 [hp_X]/1 g; ARNICA MONTANA 30 [hp_X]/1 g; FERROSOFERRIC PHOSPHATE 12 [hp_X]/1 g; ARABICA COFFEE BEAN 6 [hp_X]/1 g; MAGNESIUM PHOSPHATE, DIBASIC TRIHYDRATE 12 [hp_X]/1 g
INACTIVE INGREDIENTS: LACTOSE MONOHYDRATE; ACACIA

Hyland's Naturals Baby Oral Pain Relief Nighttime

Drug Facts

Active ingredients | Purpose
Arnica Montana 30X HPUS | sore, sensitive or swelling gums
Calcarea Carbonica 12X HPUS | teething, sore, sensitive or swelling gums
Calcarea Phosphorica 12X HPUS | teething, sensitive, swelling gums, oral pain
Chamomilla 12X HPUS | sore, sensitive or swelling gums
Coffea Cruda 6X HPUS | oral pain, irritability
Ferrum Phosphoricum 12X HPUS | oral discomfort, swelling gums
Magnesia Phosphorica 12X HPUS | oral pain, occasional sleeplessness
Silicea 12X HPUS | oral pain at night, occasional sleeplessness

"HPUS" is the Homeopathic Pharmacopoeia of the United States.

Uses

■ Helps temporarily relieve symptoms of oral pain or discomfort in children, including:
■ teething ■ gum sensitivity ■ swelling or soreness of gums
■ irritability ■ occasional sleeplessness

Warnings

Stop use and ask a doctor if

■ symptoms persist for more than 72 hours or worsen.

■ swelling increases; nasal congestion, rash or fever is present or develops.

■ irritation, pain or redness persists or worsens.

Directions

■ Use as directed.

Children under 6 months | At onset of symptoms, dissolve 2 tablets on tongue every hour up to 4 hours as needed. If symptoms persist, 2 tablets every 4 hours during the night until relieved.
Children 6 months to under 3 years | At onset of symptoms, dissolve 3 tablets on tongue every hour up to 4 hours as needed. If symptoms persist, 3 tablets every 4 hours during the night until relieved

Inactive ingredients

Acacia Gum, Lactose.

Questions?

www.hylands.com or care@hylands.com

PURPOSE

Helps temporarily relieve symptoms of oral pain or discomfort in children, including: teething, gum sensitivity, swelling or soreness of gums, irritability, occasional sleeplessness.

Principal Display Panel

Hyland's

NATURALS

•baby•

Oral Pain

Relief*

NIGHTTIME

NO BENZOCAINE,

DYES or PARABENS

Sleeplessness

Teething Pain

Oral Discomfort

Irritability

Swelling

0+ Months

125

QUICK-DISSOLVING TABLETS

HOMEOPATHIC